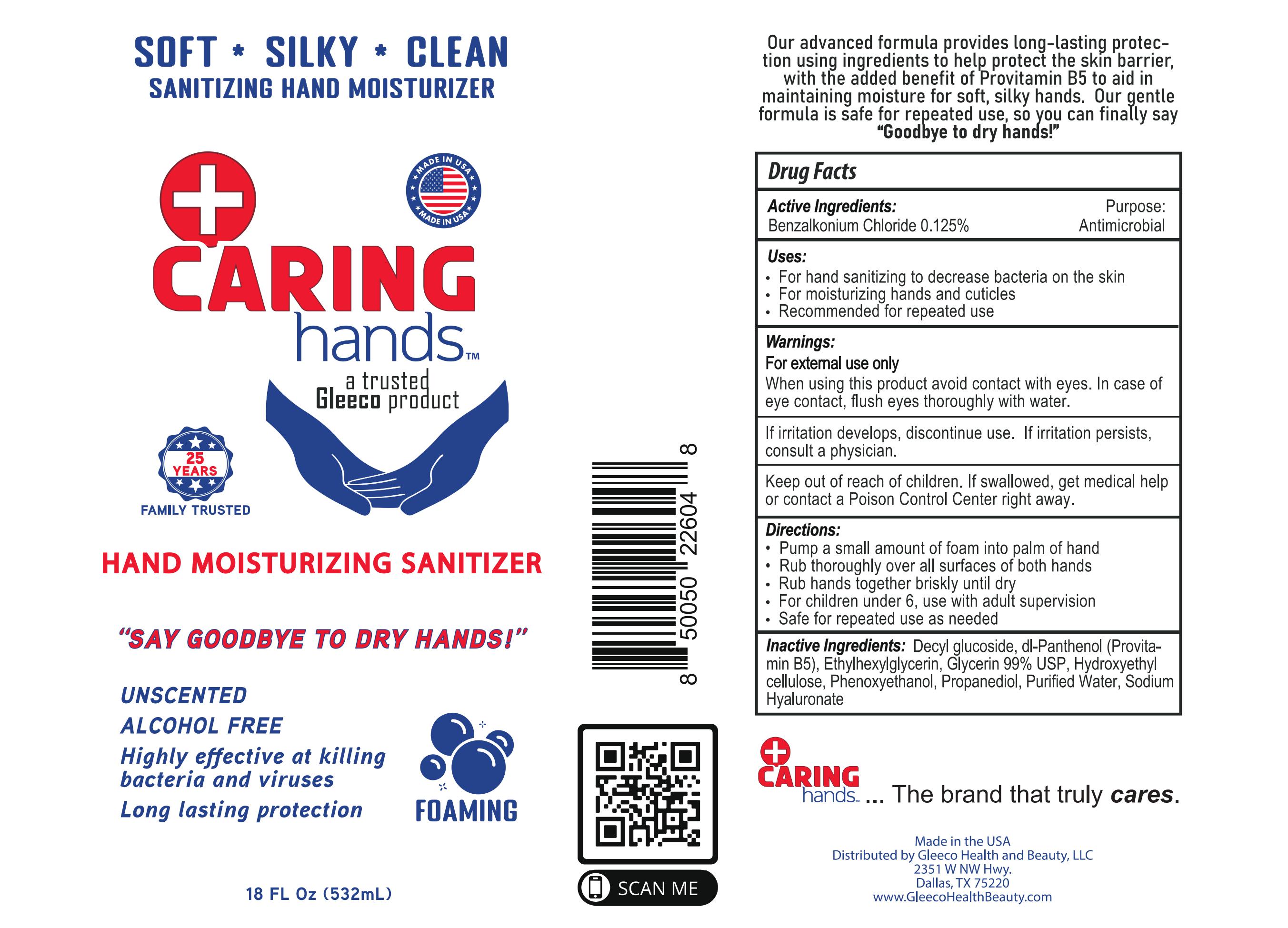 DRUG LABEL: Caring Hands
NDC: 85236-111 | Form: LIQUID
Manufacturer: Gleeco Labs LLC
Category: otc | Type: HUMAN OTC DRUG LABEL
Date: 20260114

ACTIVE INGREDIENTS: BENZALKONIUM CHLORIDE 0.125 mg/100 mL
INACTIVE INGREDIENTS: WATER; PHENOXYETHANOL; PROPANEDIOL; HYALURONATE SODIUM; ETHYLHEXYLGLYCERIN; DECYL GLUCOSIDE; PANTHENOL; HYDROXYETHYLCELLULOSE; GLYCERIN

BZK Gleeco Labs

Active Ingredient(s)

Benzalkonium chloride 0.125%

Purpose

Antimicrobial

Use

For hand sanitizing to decrease bacteria on the skin
For moisturizing hands and cuticles
Recommended for repeated use

Warnings:

For external use only

When using this product avoid contact with eyes. In case of eye contact, flush eyes thoroughly with water.

If irritation develops, discontinue use. If irritation persists, consult a physician.

KEEP OUT OF REACH OF CHILDREN

Keep children out of reach unless under adult supervision. If swallowed, get medical help or contact a poison control center right away

Directions

Pump a small amount of foam into palm of hand
Rub thoroughly over all surfaces of both hands
Rub hands together briskly until dry
For children under 6, use with adult supervision
Safe for repeated use as needed

Inactive ingredients

Decyl glucoside, dl-Panthenol (Provita-min B5), Ethylhexylglycerin, Glycerin 99% USP, Hydroxyethyl

cellulose, Phenoxyethanol, Propanediol, Purified Water, Sodium

Hyaluronate

Package Label - Principal Display Panel

532 mL, NDC: 85236-111-11